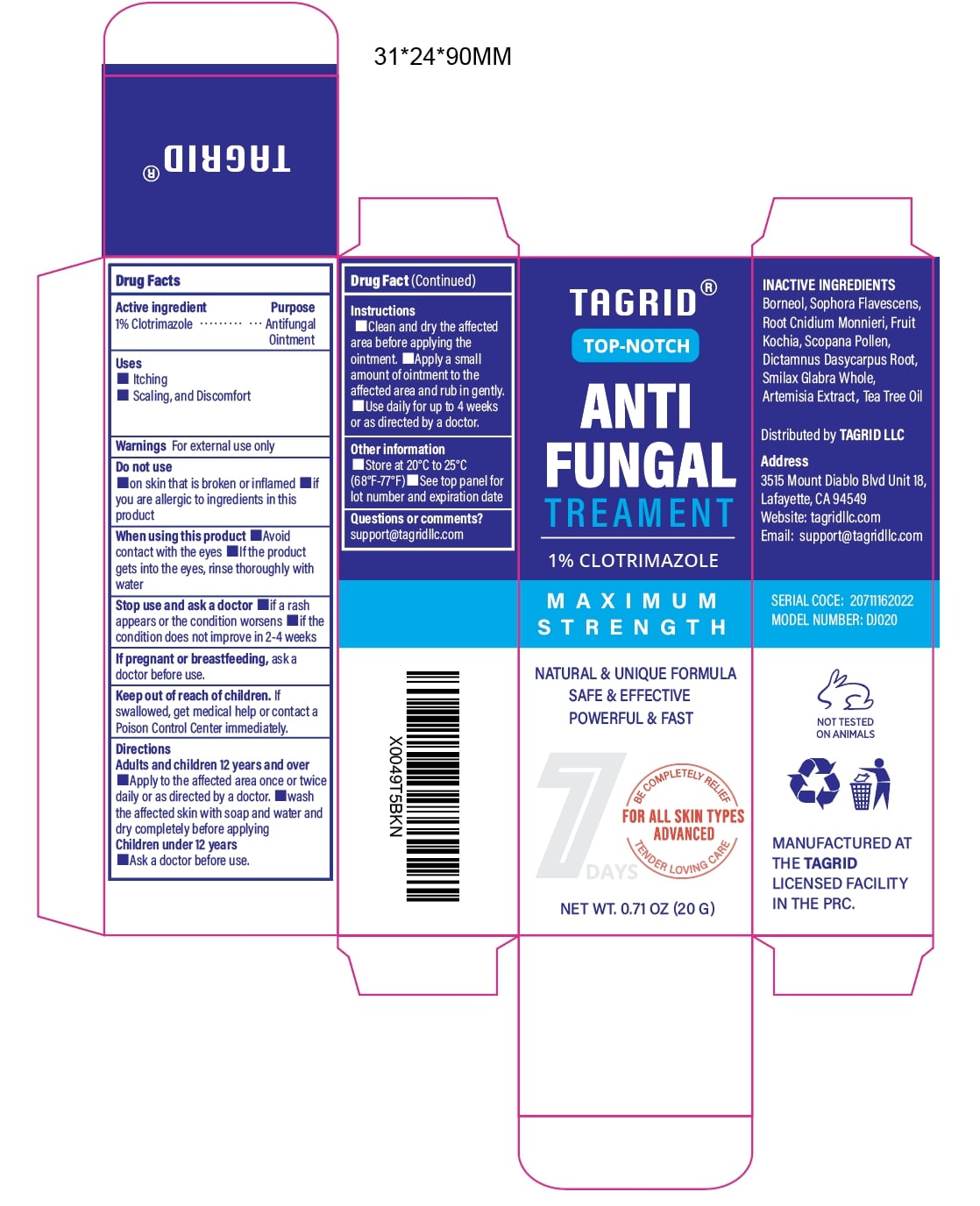 DRUG LABEL: Tagrid Antifungal Treament Clotrimazole 1%
NDC: 85384-0012 | Form: CREAM
Manufacturer: TAGRID LLC
Category: otc | Type: HUMAN OTC DRUG LABEL
Date: 20250709

ACTIVE INGREDIENTS: Clotrimazole 10 mg/1 g
INACTIVE INGREDIENTS: CNIDIUM MONNIERI FRUIT; DICTAMNUS DASYCARPUS ROOT BARK; TEA TREE OIL; BORNEOL; BASSIA SCOPARIA POLLEN; SOPHORA FLAVESCENS ROOT; BASSIA SCOPARIA FRUIT; ARTEMISIA ARGYI LEAF; SMILAX GLABRA WHOLE

ACTIVE INGREDIENT

Clotrimazole 1%

PURPOSE

Antifungal Ointment

INDICATIONS AND USAGE

Treats fungal infections of the skin, such as folliculitis, athlete's foot, jock itch, ringworm, and seborrheic dermatitis.

Effective for relieving symptoms of itching, scaling, redness, and discomfort caused by fungal infections.

Helps reduce and control fungal skin infections, including tinea corporis (body fungus), tinea cruris (groin fungus), tinea pedis (foot fungus), and tinea versicolor.

Can be used on areas prone to fungal growth, such as the scalp,face,chest, back, arms, and legs.

WARNINGS

For external use only.

DO NOT USE

on broken, inflamed, or severely irritated skin.

lf you are allergic to Clotrimazole or any other ingredients in this product.

WHEN USING

Avoid contact with the eyes. If the product gets into the eyes, rinse thoroughly with water.

Stop use and ask a doctor if: a rash appears. the condition does not improve within 2-4 weeks of regular use.

PREGNANCY OR BREAST FEEDING

ask a healthcare provider before use.

KEEP OUT OF REACH OF CHILDREN

If swallowed, get medical help or contact a Poison Control Center right away.

Directions
1. Adults and children 12 years and over:
Clean and dry the affected area before application.
Apply a small amount to the affected area once or twice daily, or as directed by a doctor.
Use continuously for up to 4 weeks, or as directed by a healthcare provider.
2. Children under 12 years:
Ask a doctor before use.

INSTRUCTIONS FOR USE

Clean the affected area thoroughly with soap and water and dry completely before applying the cream
Apply a small amount of ointment to the affected area and gently rub in.

Use daily for up to 4 weeks, or as directed by a healthcare provider.

OTHER SAFETY INFORMATION

store at 20°C to 25°C (68°F-77°F).
see the top panel for lot number and expiration date.

Questions or comments?
Contact us at: support@tagridllc.com

INACTIVE INGREDIENT

Borneol

Sophora Flavescens Root

Cnidium monnieri Root

Bassia scoparia Fruit

Scoparia Pollen
Dictamnus Dasycarpus Root
Smilax Glabra Whole

Artemisia argyi Leaf
Tea Tree Oil